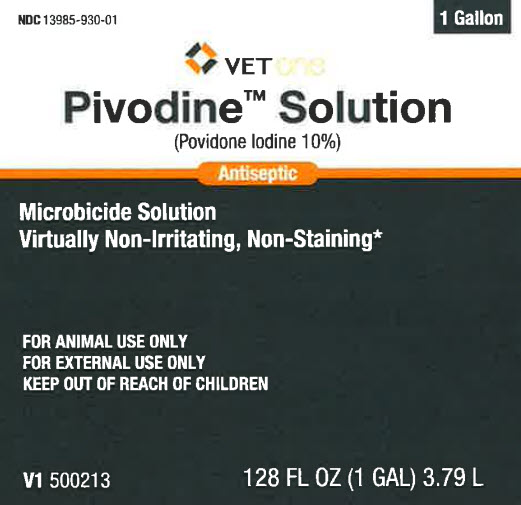 DRUG LABEL: Povidone Iodine
NDC: 13985-930 | Form: SOLUTION
Manufacturer: MWI/VETONE
Category: animal | Type: OTC ANIMAL DRUG LABEL
Date: 20250317

ACTIVE INGREDIENTS: POVIDONE-IODINE 10 mg/1 mL
INACTIVE INGREDIENTS: C12-13 PARETH-9; CITRIC ACID MONOHYDRATE; SODIUM PHOSPHATE, DIBASIC, ANHYDROUS; GLYCERIN; SODIUM HYDROXIDE; WATER

Vetone 110.000/110AA /050AE
Povidone Iodine Solution 10%

Ingredients

ACTIVE INGREDIENT: Povidone-Iodine 10% (1% available Iodine)

INACTIVE INGREDIENT: C12-13 pareth-9, citric acid, disodium phosphate, glycerin, sodium hydroxide, water

Indications and Use

INDICATIONS: Kills gram-negative and gram-positive bacteria, fungi, viruses, protozoa and yeasts. Film-forming, virtually non-irritating and non-staining to skin, hair and natural fabrics after repeated wash.

DIRECTIONS FOR USE: Apply full-strength as often as needed. Wet area thoroughly to ensure complete coverage but avoid pooling. May be covered with bandage if necessary.

Caution:

Avoid contact with eyes. May be harmful if swallowed. If infection or irritation persists, discontinue use and consult a veterinarian.

Storage

Store at controlled room temperature between 15° – 30° C (59° – 86° F). Keep container tightly closed when not in use.

Disclaimer

*after repeated wash

TAKE TIME OBSERVE LABEL DIRECTIONS

Adverse event

Distributed by: MWI

Boise, ID 83705

www.VetOne.net

Principal Panel Display

NDC 13985-930-01

VETONE

Pivodine Solution

(Povidone Iodine 10%)

Antiseptic

Microbicide Solution

Virtually Non-Irritating, Non-Staining*

FOR ANIMAL USE ONLY

FOR EXTERNAL USE ONLY

KEEP OUT OF REACH OF CHILDREN

128 FL OZ (1 GAL) 3.79 L